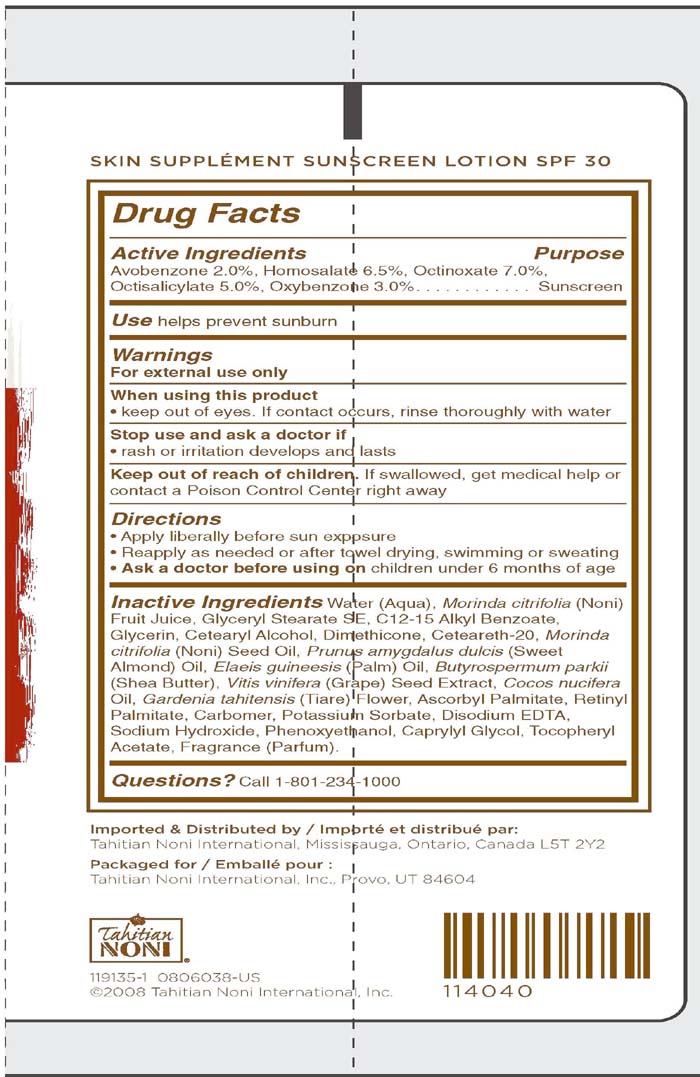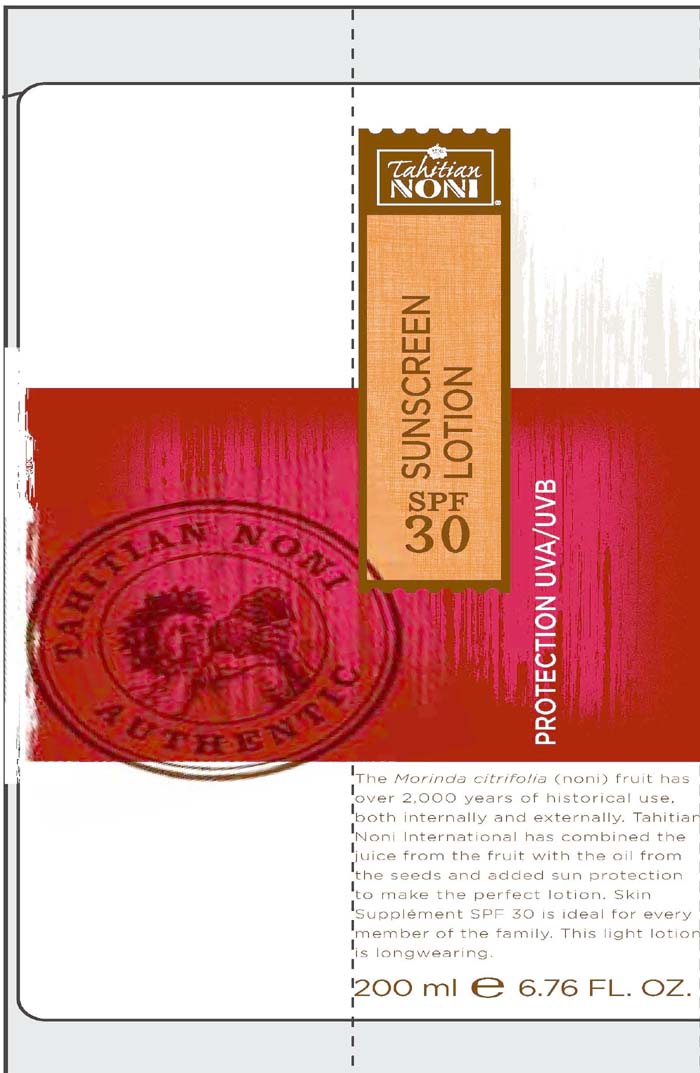 DRUG LABEL: Tahitian Noni
NDC: 44717-536 | Form: LOTION
Manufacturer: Wasatch Product Development
Category: otc | Type: HUMAN OTC DRUG LABEL
Date: 20110309

ACTIVE INGREDIENTS: AVOBENZONE 2.0 mL/100 mL; HOMOSALATE 6.5 mL/100 mL; OCTINOXATE 7.0 mL/100 mL; OCTISALATE 5.0 mL/100 mL; OXYBENZONE 3.0 mL/100 mL
INACTIVE INGREDIENTS: MORINDA CITRIFOLIA FRUIT; GLYCERYL MONOSTEARATE; ALKYL (C12-15) BENZOATE; GLYCERIN; CETOSTEARYL ALCOHOL; DIMETHICONE; MORINDA CITRIFOLIA SEED OIL; VITIS VINIFERA SEED; SHEA BUTTER; COCONUT OIL; GARDENIA TAITENSIS FLOWER; ASCORBYL PALMITATE; VITAMIN A PALMITATE; POTASSIUM SORBATE; EDETATE DISODIUM; SODIUM HYDROXIDE; PHENOXYETHANOL; CAPRYLYL GLYCOL

Sunscreen Lotion SPF 30

Active Ingredients

Avobenzone 2.0%

Homosalate 6.5%

Octinoxate 7.0%

Octisalate 5.0%

Oxybenzone 3.0%

Warnings:

-For external use only

-When using this product keep out of eyes. If contact occurs, rinse thoroughly with water

-Stop use and ask a doctor if rash or irritation develops and lasts

-Keep out of reach of children. If swallowed, get medical help or contact a Poison Control Center right away.

INDICATIONS AND USAGE

Use: helps prevent sunburn

Directions:

-apply liberally before sun exposure

-As a doctor before using on children 6 months of age

INACTIVE INGREDIENT

Inactive Ingredients: Water (Aqua), Morinda citrifolia (noni) fruit juice, glyceryl stearate SE, C12-15 Alkyl benzoate, glycerin, cetearyl alcohol, dimethicone, ceteareth-20, morinda citrifolia (noni) seed Oil, prunus amygdalus dulcis (sweet almond) Oil, elaeis guineesis (palm) oil, butyrospermum parkii (shea butter), vitis vinifera (grape) seed extract, cocous nucifera Oil, gardenia tahitensis (tiare) flower, ascorbyl palmitate, retinyl palmitate, carbomber, potassium sorbate, disodium EDTA, sodium hydroxide, phenoxyethanol, caprylyl glycol, tocopheryl acetate, fragrance (parfum).

PACKAGE LABEL

Tahitian Noni

Sunscreen Lotion SPF 30

200 mL/ 6.76 fl. oz.